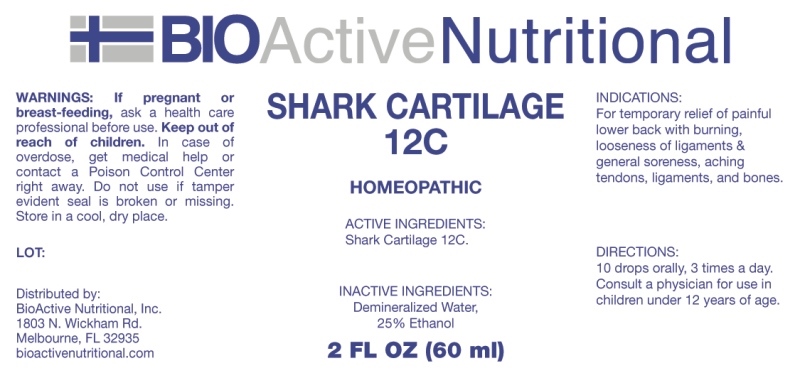 DRUG LABEL: Shark Cartilage
NDC: 43857-0633 | Form: LIQUID
Manufacturer: BioActive Nutritional, Inc.
Category: homeopathic | Type: HUMAN OTC DRUG LABEL
Date: 20230411

ACTIVE INGREDIENTS: SHARK CARTILAGE 12 [hp_C]/1 mL
INACTIVE INGREDIENTS: WATER; ALCOHOL

DRUG FACTS:

ACTIVE INGREDIENTS:

Shark Cartilage 12C.

PURPOSE:

For temporary relief of painful lower back with burning, looseness of ligaments & general soreness, aching tendons, ligaments, and bones.

WARNINGS:

If pregnant or breast-feeding, ask a health care professional before use.

Keep out of reach of children. In case of overdose, get medical help or contact a Poison Control Center right away.

Do not use if tamper evident seal is broken or missing.

Store in cool, dry place.

KEEP OUT OF REACH OF CHILDREN:

In case of overdose, get medical help or contact a Poison Control Center right away.

DIRECTIONS:

10 drops orally, 3 times a day. Consult a physician for use in children under 12 years of age.

INACTIVE INGREDIENTS:

Demineralized Water, 25% Ethanol

INDICATIONS:

For temporary relief of painful lower back with burning, looseness of ligaments & general soreness, aching tendons, ligaments, and bones.

QUESTIONS:

Distributed by:
BioActive Nutritional, Inc.
1803 N. Wickham Rd.
Melbourne, FL 32935
bioactivenutritional.com

PACKAGE LABEL DISPLAY:

BIOActive Nutritional

SHARK CARTILAGE

12C

HOMEOPATHIC

2 FL OZ (60 ml)